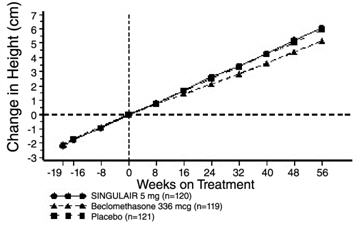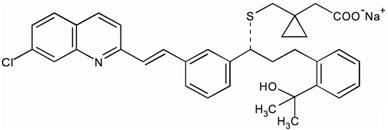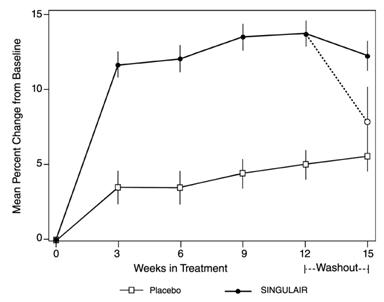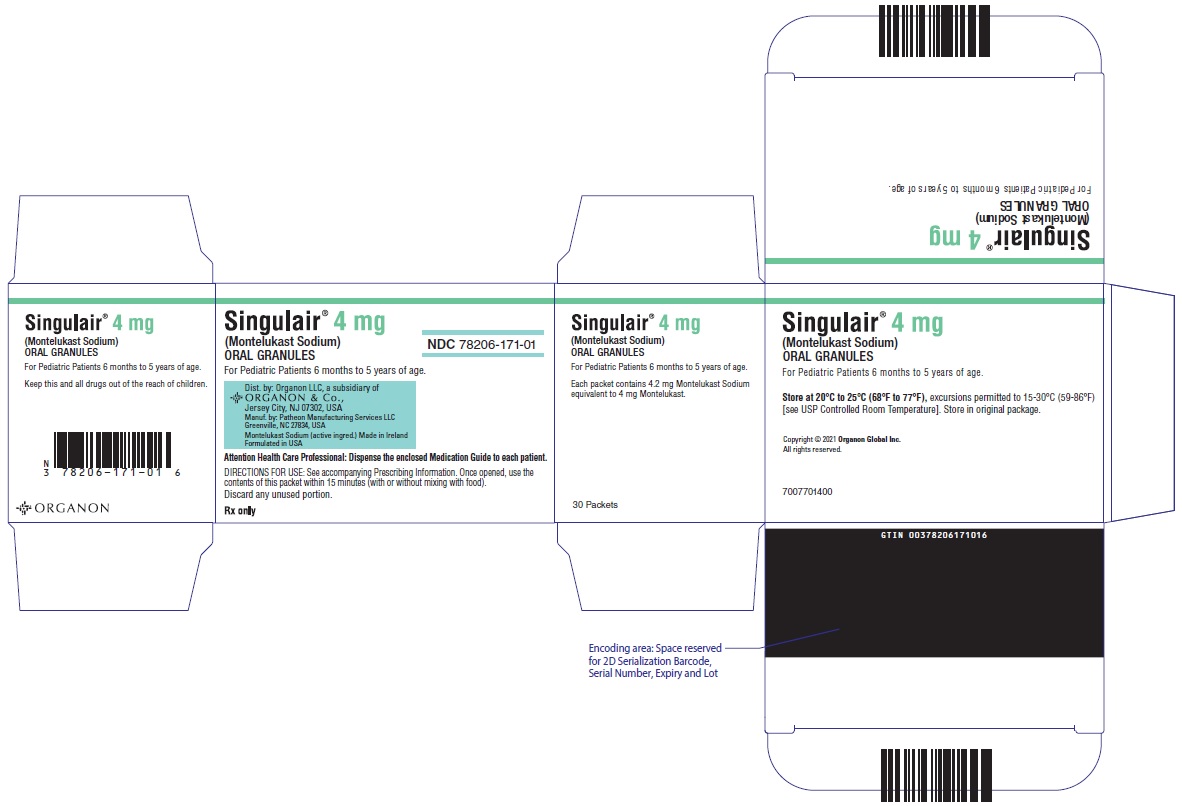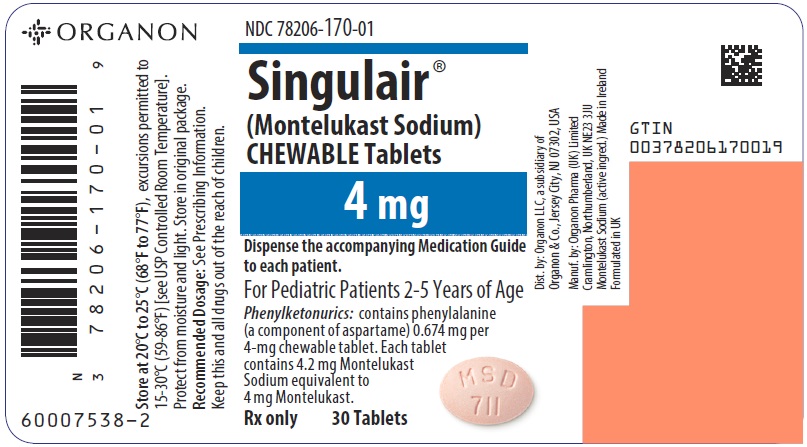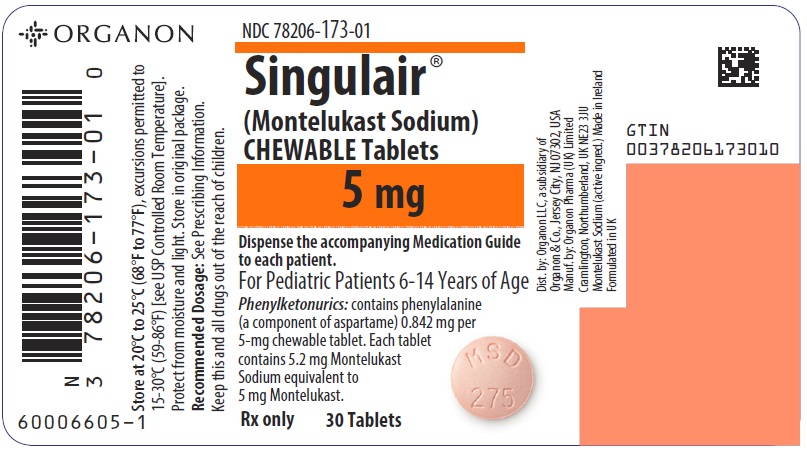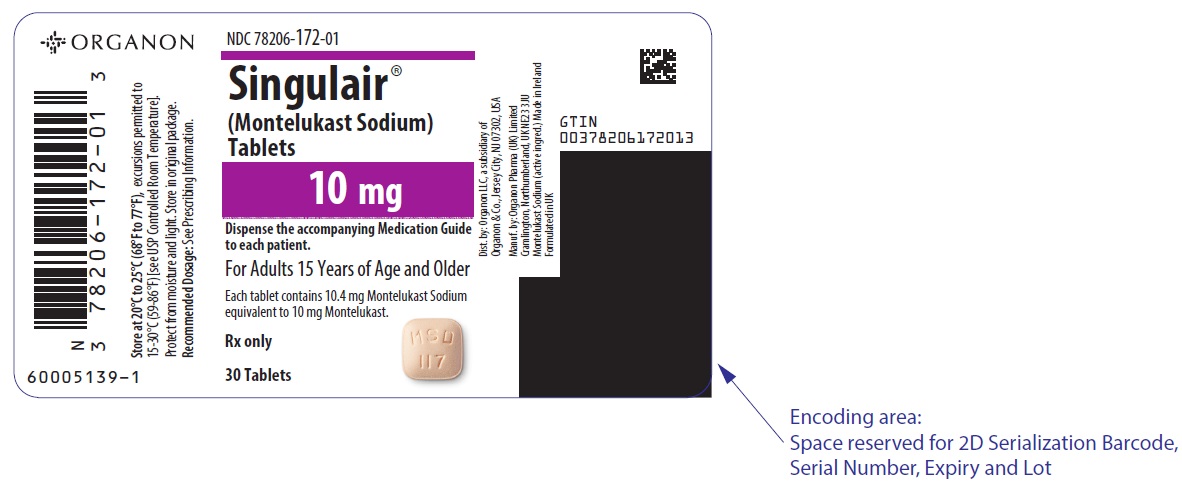 DRUG LABEL: SINGULAIR
NDC: 78206-171 | Form: GRANULE
Manufacturer: Organon LLC
Category: prescription | Type: HUMAN PRESCRIPTION DRUG LABEL
Date: 20250430

ACTIVE INGREDIENTS: MONTELUKAST SODIUM 4 mg/1 1
INACTIVE INGREDIENTS: MANNITOL; HYDROXYPROPYL CELLULOSE (1600000 WAMW); MAGNESIUM STEARATE

HIGHLIGHTS OF PRESCRIBING INFORMATION

These highlights do not include all the information needed to use SINGULAIR safely and effectively. See full prescribing information for SINGULAIR.
SINGULAIR® (montelukast sodium) tablets, for oral use
SINGULAIR® (montelukast sodium) chewable tablets, for oral use
SINGULAIR® (montelukast sodium) oral granules
Initial U.S. Approval: 1998

WARNING: SERIOUS NEUROPSYCHIATRIC EVENTS

See full prescribing information for complete boxed warning.

- Serious neuropsychiatric events have been reported in patients taking SINGULAIR (5.1).
- Discuss benefits and risks of SINGULAIR with patients and caregivers (5.1).
- Monitor for neuropsychiatric symptoms in patients taking SINGULAIR (5.1).
- Discontinue SINGULAIR immediately if neuropsychiatric symptoms occur (5.1).
- Because the benefits of SINGULAIR may not outweigh the potential risk of neuropsychiatric symptoms in patients with allergic rhinitis, reserve use for patients who have an inadequate response or intolerance to alternative therapies (1.3, 5.1).

RECENT MAJOR CHANGES

Indications and Usage (1.3, 1.4) | 02/2021
Dosage and Administration (2.1, 2.2, 2.3, 2.4) | 02/2021
Warnings and Precautions (5.1, 5.6) | 02/2021

1 INDICATIONS AND USAGE

SINGULAIR is a leukotriene receptor antagonist indicated for:

- Prophylaxis and chronic treatment of asthma in patients 12 months of age and older (1.1).
- Acute prevention of exercise-induced bronchoconstriction (EIB) in patients 6 years of age and older (1.2).
- Relief of symptoms of allergic rhinitis (AR): seasonal allergic rhinitis (SAR) in patients 2 years of age and older, and perennial allergic rhinitis (PAR) in patients 6 months of age and older. Reserve use for patients who have an inadequate response or intolerance to alternative therapies (1.3).

Limitations of Use:

- Not indicated to treat an acute asthma attack (5.2).

2 DOSAGE AND ADMINISTRATION

Administration (by indications):

- Asthma: Once daily in the evening for patients 12 months and older (2.1).
- Acute prevention of EIB: One tablet at least 2 hours before exercise for patients 6 years of age and older (2.2).
- Seasonal allergic rhinitis: Once daily for patients 2 years and older (2.3).
- Perennial allergic rhinitis: Once daily for patients 6 months and older (2.3).

Dosage (by age):

- 15 years and older: one 10-mg tablet (2).
- 6 to 14 years: one 5-mg chewable tablet (2).
- 2 to 5 years: one 4-mg chewable tablet or one packet of 4-mg oral granules (2).
- 6 to 23 months: one packet of 4-mg oral granules (2).

Patients with both asthma and allergic rhinitis should take only one dose daily in the evening (2.4). For oral granules: Must administer within 15 minutes after opening the packet (with or without mixing with food) (2.5).

3 DOSAGE FORMS AND STRENGTHS

- Tablets: 10 mg (3)
- Chewable tablets: 5 mg and 4 mg (3)
- Oral granules: 4 mg (3)

4 CONTRAINDICATIONS

Hypersensitivity to any component of SINGULAIR (4).

5 WARNINGS AND PRECAUTIONS

- Do not prescribe SINGULAIR to treat an acute asthma attack (5.2).
- Advise patients to have appropriate rescue medication available (5.2).
- Inhaled corticosteroid may be reduced gradually. Do not abruptly substitute SINGULAIR for inhaled or oral corticosteroids (5.3).
- Patients with known aspirin sensitivity should continue to avoid aspirin or non-steroidal anti-inflammatory agents while taking SINGULAIR (5.4).
- Systemic eosinophilia, sometimes presenting with clinical features of vasculitis consistent with Churg-Strauss syndrome, has been reported. These events have been sometimes associated with the reduction of oral corticosteroid therapy (5.5 and 6.2).
- Inform patients with phenylketonuria that the 4-mg and 5-mg chewable tablets contain phenylalanine (5.6).

6 ADVERSE REACTIONS

Most common adverse reactions (incidence ≥5% and greater than placebo listed in descending order of frequency): upper respiratory infection, fever, headache, pharyngitis, cough, abdominal pain, diarrhea, otitis media, influenza, rhinorrhea, sinusitis, otitis (6.1).

To report SUSPECTED ADVERSE REACTIONS, contact Organon LLC, a subsidiary of Organon & Co., Inc., at 1-844-674-3200 or FDA at 1-800-FDA-1088 or www.fda.gov/medwatch.

FULL PRESCRIBING INFORMATION

WARNING: SERIOUS NEUROPSYCHIATRIC EVENTS

Serious neuropsychiatric (NP) events have been reported with the use of SINGULAIR. The types of events reported were highly variable, and included, but were not limited to, agitation, aggression, depression, sleep disturbances, suicidal thoughts and behavior (including suicide). The mechanisms underlying NP events associated with SINGULAIR use are currently not well understood [see Warnings and Precautions (5.1)].
Because of the risk of NP events, the benefits of SINGULAIR may not outweigh the risks in some patients, particularly when the symptoms of disease may be mild and adequately treated with alternative therapies. Reserve use of SINGULAIR for patients with allergic rhinitis who have an inadequate response or intolerance to alternative therapies [see Indications and Usage (1.3)]. In patients with asthma or exercise-induced bronchoconstriction, consider the benefits and risks before prescribing SINGULAIR.
Discuss the benefits and risks of SINGULAIR with patients and caregivers when prescribing SINGULAIR. Advise patients and/or caregivers to be alert for changes in behavior or new NP symptoms when taking SINGULAIR. If changes in behavior are observed, or if new NP symptoms or suicidal thoughts and/or behavior occur, advise patients to discontinue SINGULAIR and contact a healthcare provider immediately [see Warnings and Precautions (5.1)].

1 INDICATIONS AND USAGE

1.1 Asthma

SINGULAIR® is indicated for the prophylaxis and chronic treatment of asthma in adults and pediatric patients 12 months of age and older.

1.2 Exercise-Induced Bronchoconstriction (EIB)

SINGULAIR is indicated for prevention of exercise-induced bronchoconstriction (EIB) in patients 6 years of age and older.

1.3 Allergic Rhinitis

SINGULAIR is indicated for the relief of symptoms of seasonal allergic rhinitis in patients 2 years of age and older and perennial allergic rhinitis in patients 6 months of age and older. Because the benefits of SINGULAIR may not outweigh the risk of neuropsychiatric symptoms in patients with allergic rhinitis [see Warnings and Precautions (5.1)], reserve use for patients who have an inadequate response or intolerance to alternative therapies.

1.4 Limitations of Use

SINGULAIR is not indicated for the treatment of an acute asthma attack.

2 DOSAGE AND ADMINISTRATION

2.1 Asthma

For asthma, administer SINGULAIR orally once daily in the evening, with or without food. There have been no clinical trials in patients with asthma to evaluate the relative efficacy of morning versus evening dosing.

The following doses are recommended:

Table 1: Recommended Dosage in Asthma
Age | Dose
Adult and adolescent patients 15 years of age and older | one 10 mg tablet
Pediatric patients 6 to 14 years of age | one 5 mg chewable tablet
Pediatric patients 2 to 5 years of age | one 4 mg chewable tablet or one packet of oral granules
Pediatric patients 12 to 23 months of age [Safety and effectiveness in pediatric patients less than 12 months of age with asthma have not been established.] | one packet 4 mg oral granules

Patients who miss a dose should take the next dose at their regular time and should not take 2 doses at the same time.

2.2 Exercise-Induced Bronchoconstriction (EIB)

For prevention of EIB, administer a single dose of SINGULAIR orally at least 2 hours, before exercise. The following doses are recommended:

Table 2: Recommended Dosage in Exercise-Induced Bronchoconstriction (EIB)
Age | Dose
Adult and adolescent patients 15 years of age and older | one 10 mg tablet
Pediatric patients 6 to 14 years of age [Safety and effectiveness in patients younger than 6 years of age have not been established.] | one 5 mg chewable tablet

An additional dose of SINGULAIR should not be taken within 24 hours of a previous dose. Patients already taking SINGULAIR daily for another indication (including chronic asthma) should not take an additional dose to prevent EIB. All patients should have available for rescue a short-acting β-agonist.

Daily administration of SINGULAIR for the chronic treatment of asthma has not been established to prevent acute episodes of EIB.

2.3 Allergic Rhinitis

For allergic rhinitis, administer SINGULAIR orally once daily without regard to time of food ingestion. Time of administration in patients with allergic rhinitis can be individualized to suit patient needs.

The following doses for the treatment of symptoms of seasonal allergic rhinitis are recommended:

Table 3: Recommended Dosage in Seasonal Allergic Rhinitis
Age | Dose
Adult and adolescent patients 15 years of age and older | one 10 mg tablet
Pediatric patients 6 to 14 years of age | one 5 mg chewable tablet
Pediatric patients 2 to 5 years of age [Safety and effectiveness in pediatric patients younger than 2 years of age with seasonal allergic rhinitis have not been established.] | one 4 mg chewable tablet or one packet of 4 mg oral granules

The following doses for the treatment of symptoms of perennial allergic rhinitis are recommended:

Table 4: Recommended Dosage in Perennial Allergic Rhinitis
Age | Dose
Adult and adolescent patients 15 years of age and older | one 10 mg tablet
Pediatric patients 6 to 14 years of age | one 5 mg chewable tablet
Pediatric patients 2 to 5 years of age | one 4 mg chewable tablet or one packet of 4 mg oral granules
Pediatric patients 6 to 23 months of age [Safety and effectiveness in pediatric patients younger than 6 months of age with perennial allergic rhinitis have not been established.] | one packet of 4 mg oral granules

Patients who miss a dose should take the next dose at their regular time and should not take 2 doses at the same time.

2.4 Asthma and Allergic Rhinitis

For patients with both asthma and allergic rhinitis, administer only one SINGULAIR dose orally once daily in the evening.

Patients who miss a dose should take the next dose at their regular time and should not take 2 doses at the same time.

2.5 Instructions for Administration of Oral Granules

SINGULAIR 4-mg oral granules can be administered either directly in the mouth, dissolved in 1 teaspoonful (5 mL) of cold or room temperature baby formula or breast milk, or mixed with a spoonful of cold or room temperature soft foods; based on stability studies, only applesauce, carrots, rice, or ice cream should be used. The packet should not be opened until ready to use. After opening the packet, the full dose (with or without mixing with baby formula, breast milk, or food) must be administered within 15 minutes. If mixed with baby formula, breast milk, or food, SINGULAIR oral granules must not be stored for future use. Discard any unused portion. SINGULAIR oral granules are not intended to be dissolved in any liquid other than baby formula or breast milk for administration. However, liquids may be taken subsequent to administration. SINGULAIR oral granules can be administered without regard to the time of meals.

3 DOSAGE FORMS AND STRENGTHS

- Tablets: 10 mg, beige, rounded square-shaped, film-coated tablets, with code MSD 117 on one side and SINGULAIR on the other.
- Chewable Tablets: 5 mg, pink, round, bi-convex-shaped, with code MSD 275 on one side and SINGULAIR on the other.
- Chewable Tablets: 4 mg, pink, oval, bi-convex-shaped, with code MSD 711 on one side and SINGULAIR on the other.
- Oral Granules: 4 mg, white granules with 500 mg net weight, packed in a child-resistant foil packet.

4 CONTRAINDICATIONS

SINGULAIR is contraindicated in patients with hypersensitivity to any of its components.

5 WARNINGS AND PRECAUTIONS

5.1 Neuropsychiatric Events

Serious neuropsychiatric (NP) events have been reported with use of SINGULAIR. These postmarketing reports have been highly variable and included, but were not limited to, agitation, aggressive behavior or hostility, anxiousness, depression, disorientation, disturbance in attention, dream abnormalities, dysphemia (stuttering), hallucinations, insomnia, irritability, memory impairment, obsessive-compulsive symptoms, restlessness, somnambulism, suicidal thoughts and behavior (including suicide), tic, and tremor. NP events have been reported in adult, adolescent, and pediatric patients with and without a previous history of psychiatric disorder. NP events have been reported mostly during SINGULAIR treatment, but some were reported after SINGULAIR discontinuation. Animal studies showed that montelukast distributes into the brain in rats [see Clinical Pharmacology (12.3)]; however, the mechanisms underlying SINGULAIR-associated NP events are currently not well understood. Based upon the available data, it is difficult to identify risk factors for or quantify the risk of NP events with SINGULAIR use.
Because of the risk of NP events, the benefits of SINGULAIR may not outweigh the risks in some patients, particularly when the symptoms of disease may be mild and adequately treated with alternative therapies. Reserve use of SINGULAIR for patients with allergic rhinitis who have an inadequate response or intolerance to alternative therapies [see Indications and Usage (1.3)]. In patients with asthma or exercise-induced bronchoconstriction, consider the benefits and risks before prescribing SINGULAIR.
Discuss the benefits and risks of SINGULAIR use with patients and caregivers when prescribing SINGULAIR. Advise patients and/or caregivers to be alert for changes in behavior or for new NP symptoms when taking SINGULAIR. If changes in behavior are observed, or if new NP symptoms or suicidal thoughts and/or behavior occur, advise patients to discontinue SINGULAIR and contact a healthcare provider immediately. In many cases, symptoms resolved after stopping SINGULAIR therapy; however, in some cases symptoms persisted after discontinuation of SINGULAIR. Therefore, continue to monitor and provide supportive care until symptoms resolve. Re-evaluate the benefits and risks of restarting treatment with SINGULAIR if such events occur.

5.2 Acute Asthma

SINGULAIR is not indicated for use in the reversal of bronchospasm in acute asthma attacks, including status asthmaticus. Patients should be advised to have appropriate rescue medication available. Therapy with SINGULAIR can be continued during acute exacerbations of asthma. Patients who have exacerbations of asthma after exercise should have available for rescue a short-acting inhaled β-agonist.

5.3 Concomitant Corticosteroid Use

While the dose of inhaled corticosteroid may be reduced gradually under medical supervision, SINGULAIR should not be abruptly substituted for inhaled or oral corticosteroids.

5.4 Aspirin Sensitivity

Patients with known aspirin sensitivity should continue avoidance of aspirin or non-steroidal anti-inflammatory agents while taking SINGULAIR. Although SINGULAIR is effective in improving airway function in asthmatics with documented aspirin sensitivity, it has not been shown to truncate bronchoconstrictor response to aspirin and other non-steroidal anti-inflammatory drugs in aspirin-sensitive asthmatic patients [see Clinical Studies (14.1)].

5.5 Eosinophilic Conditions

Patients with asthma on therapy with SINGULAIR may present with systemic eosinophilia, sometimes presenting with clinical features of vasculitis consistent with Churg-Strauss syndrome, a condition which is often treated with systemic corticosteroid therapy. These events have been sometimes associated with the reduction of oral corticosteroid therapy. Physicians should be alert to eosinophilia, vasculitic rash, worsening pulmonary symptoms, cardiac complications, and/or neuropathy presenting in their patients. A causal association between SINGULAIR and these underlying conditions has not been established [see Adverse Reactions (6.2)].

5.6 Risk in Patients with Phenylketonuria

SINGULAIR contains aspartame, a source of phenylalanine. Phenylalanine can be harmful to patients with phenylketonuria (PKU). Each 4 mg and 5 mg chewable tablet contains 0.674 mg and 0.842 mg of phenylalanine, respectively. Before prescribing SINGULAIR to a patient with PKU, consider the combined daily amount of phenylalanine from all sources, including SINGULAIR.

6 ADVERSE REACTIONS

The following clinically significant adverse reactions are described elsewhere in the labeling:

- Neuropsychiatric Events [see Warnings and Precautions (5.1)]

6.1 Clinical Trials Experience

Because clinical trials are conducted under widely varying conditions, adverse reaction rates observed in the clinical trials of a drug cannot be directly compared to rates in the clinical trials of another drug and may not reflect the rates observed in clinical practice. In the following description of clinical trials experience, adverse reactions are listed regardless of causality assessment.

The most common adverse reactions (incidence ≥5% and greater than placebo; listed in descending order of frequency) in controlled clinical trials were: upper respiratory infection, fever, headache, pharyngitis, cough, abdominal pain, diarrhea, otitis media, influenza, rhinorrhea, sinusitis, otitis.

Adults and Adolescents 15 Years of Age and Older with Asthma

SINGULAIR has been evaluated for safety in approximately 2950 adult and adolescent patients 15 years of age and older in clinical trials. In placebo-controlled clinical trials, the following adverse reactions reported with SINGULAIR occurred in greater than or equal to 1% of patients and at an incidence greater than that in patients treated with placebo:

Table 5: Adverse Reactions Occurring in ≥1% of Patients with an Incidence Greater than that in Patients Treated with Placebo
 | SINGULAIR 10 mg/day (%) (n=1955) | Placebo (%) (n=1180)
Body As A Whole Pain, abdominal Asthenia/fatigue Fever Trauma | 2.9 1.8 1.5 1.0 | 2.5 1.2 0.9 0.8
Digestive System Disorders Dyspepsia Pain, dental Gastroenteritis, infectious | 2.1 1.7 1.5 | 1.1 1.0 0.5
Nervous System/Psychiatric Headache Dizziness | 18.4 1.9 | 18.1 1.4
Respiratory System Disorders Influenza Cough Congestion, nasal | 4.2 2.7 1.6 | 3.9 2.4 1.3
Skin/Skin Appendages Disorder Rash | 1.6 | 1.2
Laboratory Adverse Reactions [Number of patients tested (SINGULAIR and placebo, respectively): ALT and AST, 1935, 1170; pyuria, 1924, 1159.] ALT increased AST increased Pyuria | 2.1 1.6 1.0 | 2.0 1.2 0.9

The frequency of less common adverse reactions was comparable between SINGULAIR and placebo.

The safety profile of SINGULAIR, when administered as a single dose for prevention of EIB in adult and adolescent patients 15 years of age and older, was consistent with the safety profile previously described for SINGULAIR.

Cumulatively, 569 patients were treated with SINGULAIR for at least 6 months, 480 for one year, and 49 for two years in clinical trials. With prolonged treatment, the adverse reaction profile did not significantly change.

Pediatric Patients 6 to 14 Years of Age with Asthma

SINGULAIR has been evaluated for safety in 476 pediatric patients 6 to 14 years of age. Cumulatively, 289 pediatric patients were treated with SINGULAIR for at least 6 months, and 241 for one year or longer in clinical trials. The safety profile of SINGULAIR in the 8-week, double-blind, pediatric efficacy trial was generally similar to the adult safety profile. In pediatric patients 6 to 14 years of age receiving SINGULAIR, the following reactions occurred with a frequency ≥2% and more frequently than in pediatric patients who received placebo: pharyngitis, influenza, fever, sinusitis, nausea, diarrhea, dyspepsia, otitis, viral infection, and laryngitis. The frequency of less common adverse reactions was comparable between SINGULAIR and placebo. With prolonged treatment, the adverse reaction profile did not significantly change.

The safety profile of SINGULAIR, when administered as a single dose for prevention of EIB in pediatric patients 6 years of age and older, was consistent with the safety profile previously described for SINGULAIR.

In studies evaluating growth rate, the safety profile in these pediatric patients was consistent with the safety profile previously described for SINGULAIR. In a 56-week, double-blind study evaluating growth rate in pediatric patients 6 to 8 years of age receiving SINGULAIR, the following reactions not previously observed with the use of SINGULAIR in this age group occurred with a frequency ≥2% and more frequently than in pediatric patients who received placebo: headache, rhinitis (infective), varicella, gastroenteritis, atopic dermatitis, acute bronchitis, tooth infection, skin infection, and myopia.

Pediatric Patients 2 to 5 Years of Age with Asthma

SINGULAIR has been evaluated for safety in 573 pediatric patients 2 to 5 years of age in single- and multiple-dose studies. Cumulatively, 426 pediatric patients 2 to 5 years of age were treated with SINGULAIR for at least 3 months, 230 for 6 months or longer, and 63 patients for one year or longer in clinical trials. In pediatric patients 2 to 5 years of age receiving SINGULAIR, the following reactions occurred with a frequency ≥2% and more frequently than in pediatric patients who received placebo: fever, cough, abdominal pain, diarrhea, headache, rhinorrhea, sinusitis, otitis, influenza, rash, ear pain, gastroenteritis, eczema, urticaria, varicella, pneumonia, dermatitis, and conjunctivitis.

Pediatric Patients 6 to 23 Months of Age with Asthma

Safety and effectiveness in pediatric patients younger than 12 months of age with asthma have not been established.

SINGULAIR has been evaluated for safety in 175 pediatric patients 6 to 23 months of age. The safety profile of SINGULAIR in a 6-week, double-blind, placebo-controlled clinical study was generally similar to the safety profile in adults and pediatric patients 2 to 14 years of age. In pediatric patients 6 to 23 months of age receiving SINGULAIR, the following reactions occurred with a frequency ≥2% and more frequently than in pediatric patients who received placebo: upper respiratory infection, wheezing; otitis media; pharyngitis, tonsillitis, cough; and rhinitis. The frequency of less common adverse reactions was comparable between SINGULAIR and placebo.

Adults and Adolescents 15 Years of Age and Older with Seasonal Allergic Rhinitis

SINGULAIR has been evaluated for safety in 2199 adult and adolescent patients 15 years of age and older in clinical trials. SINGULAIR administered once daily in the morning or in the evening had a safety profile similar to that of placebo. In placebo-controlled clinical trials, the following reaction was reported with SINGULAIR with a frequency ≥1% and at an incidence greater than placebo: upper respiratory infection, 1.9% of patients receiving SINGULAIR vs. 1.5% of patients receiving placebo. In a 4-week, placebo-controlled clinical study, the safety profile was consistent with that observed in 2-week studies. The incidence of somnolence was similar to that of placebo in all studies.

Pediatric Patients 2 to 14 Years of Age with Seasonal Allergic Rhinitis

SINGULAIR has been evaluated in 280 pediatric patients 2 to 14 years of age in a 2-week, multicenter, double-blind, placebo-controlled, parallel-group safety study. SINGULAIR administered once daily in the evening had a safety profile similar to that of placebo. In this study, the following reactions occurred with a frequency ≥2% and at an incidence greater than placebo: headache, otitis media, pharyngitis, and upper respiratory infection.

Adults and Adolescents 15 Years of Age and Older with Perennial Allergic Rhinitis

SINGULAIR has been evaluated for safety in 3357 adult and adolescent patients 15 years of age and older with perennial allergic rhinitis of whom 1632 received SINGULAIR in two, 6-week, clinical studies. SINGULAIR administered once daily had a safety profile consistent with that observed in patients with seasonal allergic rhinitis and similar to that of placebo. In these two studies, the following reactions were reported with SINGULAIR with a frequency ≥1% and at an incidence greater than placebo: sinusitis, upper respiratory infection, sinus headache, cough, epistaxis, and increased ALT. The incidence of somnolence was similar to that of placebo.

Pediatric Patients 6 Months to 14 Years of Age with Perennial Allergic Rhinitis

The safety in patients 2 to 14 years of age with perennial allergic rhinitis is supported by the safety in patients 2 to 14 years of age with seasonal allergic rhinitis. The safety in patients 6 to 23 months of age is supported by data from pharmacokinetic and safety and efficacy studies in asthma in this pediatric population and from adult pharmacokinetic studies.

6.2 Postmarketing Experience

The following adverse reactions have been identified during post-approval use of SINGULAIR. Because these reactions are reported voluntarily from a population of uncertain size, it is not always possible to reliably estimate their frequency or establish a causal relationship to drug exposure.

Blood and lymphatic system disorders
increased bleeding tendency, thrombocytopenia

Immune system disorders
hypersensitivity reactions including anaphylaxis, hepatic eosinophilic infiltration

Psychiatric disorders
including, but not limited to, agitation, aggressive behavior or hostility, anxiousness, depression, disorientation, disturbance in attention, dream abnormalities, dysphemia (stuttering), hallucinations, insomnia, irritability, memory impairment, obsessive-compulsive symptoms, restlessness, somnambulism, suicidal thinking and behavior (including suicide), tic, and tremor [see Boxed Warning, Warnings and Precautions (5.1)]

Nervous system disorders
drowsiness, paraesthesia/hypoesthesia, seizures

Cardiac disorders
palpitations

Respiratory, thoracic and mediastinal disorders
epistaxis, pulmonary eosinophilia

Gastrointestinal disorders
diarrhea, dyspepsia, nausea, pancreatitis, vomiting

Hepatobiliary disorders
Cases of cholestatic hepatitis, hepatocellular liver-injury, and mixed-pattern liver injury have been reported in patients treated with SINGULAIR. Most of these occurred in combination with other confounding factors, such as use of other medications, or when SINGULAIR was administered to patients who had underlying potential for liver disease such as alcohol use or other forms of hepatitis.

Skin and subcutaneous tissue disorders
angioedema, bruising, erythema multiforme, erythema nodosum, pruritus, Stevens-Johnson syndrome/toxic epidermal necrolysis, urticaria

Musculoskeletal and connective tissue disorders
arthralgia, myalgia including muscle cramps

Renal and urinary disorders
enuresis in children

General disorders and administration site conditions
edema

Patients with asthma on therapy with SINGULAIR may present with systemic eosinophilia, sometimes presenting with clinical features of vasculitis consistent with Churg-Strauss syndrome, a condition which is often treated with systemic corticosteroid therapy. These reactions have been sometimes associated with the reduction of oral corticosteroid therapy. Physicians should be alert to eosinophilia, vasculitic rash, worsening pulmonary symptoms, cardiac complications, and/or neuropathy presenting in their patients [see Warnings and Precautions (5.5)].

7 DRUG INTERACTIONS

No dose adjustment is needed when SINGULAIR is co-administered with theophylline, prednisone, prednisolone, oral contraceptives, fexofenadine, digoxin, warfarin, gemfibrozil, itraconazole, thyroid hormones, sedative hypnotics, non-steroidal anti-inflammatory agents, benzodiazepines, decongestants, and Cytochrome P450 (CYP) enzyme inducers [see Clinical Pharmacology (12.3)].

8 USE IN SPECIFIC POPULATIONS

8.1 Pregnancy

Risk Summary

Available data from published prospective and retrospective cohort studies over decades with montelukast use in pregnant women have not established a drug-associated risk of major birth defects [see Data]. In animal reproduction studies, no adverse developmental effects were observed with oral administration of montelukast to pregnant rats and rabbits during organogenesis at doses approximately 100 and 110 times, respectively, the maximum recommended human daily oral dose (MRHDOD) based on AUCs [see Data].

The estimated background risk of major birth defects and miscarriage for the indicated population is unknown. All pregnancies have a background risk of birth defect, loss, or other adverse outcomes. In the U.S. general population, the estimated background risk of major birth defects and miscarriage in clinically recognized pregnancies is 2-4% and 15-20%, respectively.

Clinical Considerations

Disease-associated maternal and/or embryo/fetal risk

Poorly or moderately controlled asthma in pregnancy increases the maternal risk of perinatal adverse outcomes such as preeclampsia and infant prematurity, low birth weight, and small for gestational age.

Data

Human Data

Published data from prospective and retrospective cohort studies have not identified an association with SINGULAIR use during pregnancy and major birth defects. Available studies have methodologic limitations, including small sample size, in some cases retrospective data collection, and inconsistent comparator groups.

Animal Data

In embryo-fetal development studies, montelukast administered to pregnant rats and rabbits during organogenesis (gestation days 6 to 17 in rats and 6 to 18 in rabbits) did not cause any adverse developmental effects at maternal oral doses up to 400 and 300 mg/kg/day in rats and rabbits, respectively (approximately 100 and 110 times the AUC in humans at the MRHDOD, respectively).

8.2 Lactation

Risk Summary

A published clinical lactation study reports the presence of montelukast in human milk. Data available on the effects of the drug on infants, either directly [see Use in Specific Populations (8.4)] or through breast milk, do not suggest a significant risk of adverse reactions from exposure to SINGULAIR. The effects of the drug on milk production are unknown. The developmental and health benefits of breastfeeding should be considered along with the mother's clinical need for SINGULAIR and any potential adverse reactions on the breastfed infant from SINGULAIR or from the underlying maternal condition.

8.4 Pediatric Use

Safety and effectiveness of SINGULAIR for asthma have been established in pediatric patients 6 to 14 years of age. Use of SINGULAIR for this indication is supported by evidence from well-controlled studies. Safety and efficacy data in this age group are similar to those seen in adults [see Adverse Reactions (6.1), Clinical Pharmacology, Specific Populations (12.3), and Clinical Studies (14.1, 14.2)].

The effectiveness of SINGULAIR for the treatment of seasonal allergic rhinitis in pediatric patients 2 to 14 years of age and for the treatment of perennial allergic rhinitis in pediatric patients 6 months to 14 years of age have been established and is supported by extrapolation from the demonstrated effectiveness in patients 15 years of age and older with allergic rhinitis as well as the assumption that the disease course, pathophysiology and the drug’s effect are substantially similar among these populations.

The safety of SINGULAIR 4-mg chewable tablets in pediatric patients 2 to 5 years of age with asthma has been demonstrated by adequate and well-controlled data [see Adverse Reactions (6.1)]. Effectiveness of SINGULAIR in this age group is extrapolated from the demonstrated effectiveness in patients 6 years of age and older with asthma and is based on similar pharmacokinetic data, as well as the assumption that the disease course, pathophysiology and the drug’s effect are substantially similar among these populations. Effectiveness in this age group is supported by exploratory efficacy assessments from a large, well-controlled safety study conducted in patients 2 to 5 years of age.

The safety of SINGULAIR 4-mg oral granules in pediatric patients 12 to 23 months of age with asthma has been demonstrated in an analysis of 172 pediatric patients, 124 of whom were treated with SINGULAIR, in a 6-week, double-blind, placebo-controlled study [see Adverse Reactions (6.1)]. Effectiveness of SINGULAIR in this age group is extrapolated from the demonstrated effectiveness in patients 6 years of age and older with asthma based on similar mean systemic exposure (AUC), and that the disease course, pathophysiology and the drug's effect are substantially similar among these populations, supported by efficacy data from a safety trial in which efficacy was an exploratory assessment.

The safety of SINGULAIR 4-mg and 5-mg chewable tablets in pediatric patients aged 2 to 14 years with allergic rhinitis is supported by data from studies conducted in pediatric patients aged 2 to 14 years with asthma. A safety study in pediatric patients 2 to 14 years of age with seasonal allergic rhinitis demonstrated a similar safety profile [see Adverse Reactions (6.1)]. The safety of SINGULAIR 4-mg oral granules in pediatric patients as young as 6 months of age with perennial allergic rhinitis is supported by extrapolation from safety data obtained from studies conducted in pediatric patients 6 months to 23 months of age with asthma and from pharmacokinetic data comparing systemic exposures in patients 6 months to 23 months of age to systemic exposures in adults.

The safety and effectiveness in pediatric patients below the age of 12 months with asthma, 6 months with perennial allergic rhinitis, and 6 years with exercise-induced bronchoconstriction have not been established.

Growth Rate in Pediatric Patients

A 56-week, multi-center, double-blind, randomized, active- and placebo-controlled parallel group study was conducted to assess the effect of SINGULAIR on growth rate in 360 patients with mild asthma, aged 6 to 8 years. Treatment groups included SINGULAIR 5 mg once daily, placebo, and beclomethasone dipropionate administered as 168 mcg twice daily with a spacer device. For each subject, a growth rate was defined as the slope of a linear regression line fit to the height measurements over 56 weeks. The primary comparison was the difference in growth rates between SINGULAIR and placebo groups. Growth rates, expressed as least-squares (LS) mean (95% CI) in cm/year, for the SINGULAIR, placebo, and beclomethasone treatment groups were 5.67 (5.46, 5.88), 5.64 (5.42, 5.86), and 4.86 (4.64, 5.08), respectively. The differences in growth rates, expressed as least-squares (LS) mean (95% CI) in cm/year, for SINGULAIR minus placebo, beclomethasone minus placebo, and SINGULAIR minus beclomethasone treatment groups were 0.03 (-0.26, 0.31), -0.78 (-1.06, -0.49); and 0.81 (0.53, 1.09), respectively. Growth rate (expressed as mean change in height over time) for each treatment group is shown in FIGURE 1.

Figure 1: Change in Height (cm) from Randomization Visit by Scheduled Week (Treatment Group Mean ± Standard Error [The standard errors of the treatment group means in change in height are too small to be visible on the plot] of the Mean)

8.5 Geriatric Use

Of the total number of subjects in clinical studies of montelukast, 3.5% were 65 years of age and over, and 0.4% were 75 years of age and over. No overall differences in safety or effectiveness were observed between these subjects and younger subjects, and other reported clinical experience has not identified differences in responses between the elderly and younger patients, but greater sensitivity of some older individuals cannot be ruled out. The pharmacokinetic profile and the oral bioavailability of a single 10-mg oral dose of montelukast are similar in elderly and younger adults. The plasma half-life of montelukast is slightly longer in the elderly. No dosage adjustment in the elderly is required.

8.6 Hepatic Impairment

No dosage adjustment is recommended in patients with mild-to-moderate hepatic insufficiency [see Clinical Pharmacology (12.3)].

8.7 Renal Impairment

No dosage adjustment is recommended in patients with renal insufficiency [see Clinical Pharmacology (12.3)].

10 OVERDOSAGE

No specific information is available on the treatment of overdosage with SINGULAIR. In the event of overdose, it is reasonable to employ the usual supportive measures; e.g., remove unabsorbed material from the gastrointestinal tract, employ clinical monitoring, and institute supportive therapy, if required. It is not known whether montelukast is removed by peritoneal dialysis or hemodialysis.

11 DESCRIPTION

Montelukast sodium, the active ingredient in SINGULAIR, is a selective and orally active leukotriene receptor antagonist that inhibits the cysteinyl leukotriene CysLT1 receptor.

Montelukast sodium is described chemically as [R-(E)]-1-[[[1-[3-[2-(7-chloro-2-quinolinyl)ethenyl]phenyl]-3-[2-(1-hydroxy-1-methylethyl)phenyl]propyl]thio]methyl]cyclopropaneacetic acid, monosodium salt.

The empirical formula is C35H35ClNNaO3S, and its molecular weight is 608.18. The structural formula is:

Montelukast sodium is a hygroscopic, optically active, white to off-white powder. Montelukast sodium is freely soluble in ethanol, methanol, and water and practically insoluble in acetonitrile.

Each 10-mg film-coated SINGULAIR tablet contains 10.4 mg montelukast sodium, which is equivalent to 10 mg of montelukast, and the following inactive ingredients: microcrystalline cellulose, lactose monohydrate, croscarmellose sodium, hydroxypropyl cellulose, and magnesium stearate. The film coating consists of: hydroxypropyl methylcellulose, hydroxypropyl cellulose, titanium dioxide, red ferric oxide, yellow ferric oxide, and carnauba wax.

Each 4-mg and 5-mg chewable SINGULAIR tablet contains 4.2 and 5.2 mg montelukast sodium, respectively, which are equivalent to 4 and 5 mg of montelukast, respectively. Both chewable tablets contain the following inactive ingredients: mannitol, microcrystalline cellulose, hydroxypropyl cellulose, red ferric oxide, croscarmellose sodium, cherry flavor, aspartame, and magnesium stearate.

Each packet of SINGULAIR 4-mg oral granules contains 4.2 mg montelukast sodium, which is equivalent to 4 mg of montelukast. The oral granule formulation contains the following inactive ingredients: mannitol, hydroxypropyl cellulose, and magnesium stearate.

12 CLINICAL PHARMACOLOGY

12.1 Mechanism of Action

The cysteinyl leukotrienes (LTC4, LTD4, LTE4) are products of arachidonic acid metabolism and are released from various cells, including mast cells and eosinophils. These eicosanoids bind to cysteinyl leukotriene (CysLT) receptors. The CysLT type-1 (CysLT1) receptor is found in the human airway (including airway smooth muscle cells and airway macrophages) and on other pro-inflammatory cells (including eosinophils and certain myeloid stem cells). CysLTs have been correlated with the pathophysiology of asthma and allergic rhinitis. In asthma, leukotriene-mediated effects include airway edema, smooth muscle contraction, and altered cellular activity associated with the inflammatory process. In allergic rhinitis, CysLTs are released from the nasal mucosa after allergen exposure during both early- and late-phase reactions and are associated with symptoms of allergic rhinitis.

Montelukast is an orally active compound that binds with high affinity and selectivity to the CysLT1 receptor (in preference to other pharmacologically important airway receptors, such as the prostanoid, cholinergic, or β-adrenergic receptor). Montelukast inhibits physiologic actions of LTD4 at the CysLT1 receptor without any agonist activity.

12.2 Pharmacodynamics

Montelukast causes inhibition of airway cysteinyl leukotriene receptors as demonstrated by the ability to inhibit bronchoconstriction due to inhaled LTD4 in asthmatics. Doses as low as 5 mg cause substantial blockage of LTD4-induced bronchoconstriction. In a placebo-controlled, crossover study (n=12), SINGULAIR inhibited early- and late-phase bronchoconstriction due to antigen challenge by 75% and 57%, respectively.

The effect of SINGULAIR on eosinophils in the peripheral blood was examined in clinical trials. In patients with asthma aged 2 years and older who received SINGULAIR, a decrease in mean peripheral blood eosinophil counts ranging from 9% to 15% was noted, compared with placebo, over the double-blind treatment periods. In patients with seasonal allergic rhinitis aged 15 years and older who received SINGULAIR, a mean increase of 0.2% in peripheral blood eosinophil counts was noted, compared with a mean increase of 12.5% in placebo-treated patients, over the double-blind treatment periods; this reflects a mean difference of 12.3% in favor of SINGULAIR. The relationship between these observations and the clinical benefits of montelukast noted in the clinical trials is not known [see Clinical Studies (14)].

12.3 Pharmacokinetics

Absorption

Montelukast is rapidly absorbed following oral administration. After administration of the 10-mg film-coated tablet to fasted adults, the mean peak montelukast plasma concentration (Cmax) is achieved in 3 to 4 hours (Tmax). The mean oral bioavailability is 64%. The oral bioavailability and Cmax are not influenced by a standard meal in the morning.

For the 5-mg chewable tablet, the mean Cmax is achieved in 2 to 2.5 hours after administration to adults in the fasted state. The mean oral bioavailability is 73% in the fasted state versus 63% when administered with a standard meal in the morning.

For the 4-mg chewable tablet, the mean Cmax is achieved 2 hours after administration in pediatric patients 2 to 5 years of age in the fasted state.

The 4-mg oral granule formulation is bioequivalent to the 4-mg chewable tablet when administered to adults in the fasted state. The co-administration of the oral granule formulation with applesauce did not have a clinically significant effect on the pharmacokinetics of montelukast. A high fat meal in the morning did not affect the AUC of montelukast oral granules; however, the meal decreased Cmax by 35% and prolonged Tmax from 2.3 ± 1.0 hours to 6.4 ± 2.9 hours.

The safety and effectiveness of SINGULAIR in patients with asthma were demonstrated in clinical trials in which the 10-mg film-coated tablet and 5-mg chewable tablet formulations were administered in the evening without regard to the time of food ingestion. The safety of SINGULAIR in patients with asthma was also demonstrated in clinical trials in which the 4-mg chewable tablet and 4-mg oral granule formulations were administered in the evening without regard to the time of food ingestion. The safety and effectiveness of SINGULAIR in patients with seasonal allergic rhinitis were demonstrated in clinical trials in which the 10-mg film-coated tablet was administered in the morning or evening without regard to the time of food ingestion.

The comparative pharmacokinetics of montelukast when administered as two 5-mg chewable tablets versus one 10-mg film-coated tablet have not been evaluated.

Distribution

Montelukast is more than 99% bound to plasma proteins. The steady state volume of distribution of montelukast averages 8 to 11 liters. Orally administered montelukast distributes into the brain in rats.

Elimination

The plasma clearance of montelukast averages 45 mL/min in healthy adults. Following an oral dose of radiolabeled montelukast, 86% of the radioactivity was recovered in 5-day fecal collections and <0.2% was recovered in urine. Coupled with estimates of montelukast oral bioavailability, this indicates that montelukast and its metabolites are excreted almost exclusively via the bile.

In several studies, the mean plasma half-life of montelukast ranged from 2.7 to 5.5 hours in healthy young adults. The pharmacokinetics of montelukast are nearly linear for oral doses up to 50 mg. During once-daily dosing with 10-mg montelukast, there is little accumulation of the parent drug in plasma (14%).

Metabolism

Montelukast is extensively metabolized. In studies with therapeutic doses, plasma concentrations of metabolites of montelukast are undetectable at steady state in adults and pediatric patients.

In vitro studies using human liver microsomes indicate that CYP3A4, 2C8, and 2C9 are involved in the metabolism of montelukast. At clinically relevant concentrations, 2C8 appears to play a major role in the metabolism of montelukast.

Specific Populations

Patients with Hepatic Impairment
Patients with mild-to-moderate hepatic insufficiency and clinical evidence of cirrhosis had evidence of decreased metabolism of montelukast resulting in 41% (90% CI=7%, 85%) higher mean montelukast AUC following a single 10-mg dose. The elimination of montelukast was slightly prolonged compared with that in healthy subjects (mean half-life, 7.4 hours). No dosage adjustment is required in patients with mild-to-moderate hepatic insufficiency. The pharmacokinetics of SINGULAIR in patients with more severe hepatic impairment or with hepatitis have not been evaluated.

Patients with Renal Impairment
Since montelukast and its metabolites are not excreted in the urine, the pharmacokinetics of montelukast were not evaluated in patients with renal insufficiency. No dosage adjustment is recommended in these patients.

Male and Female Patients
The pharmacokinetics of montelukast are similar in males and females.

Racial Groups
Pharmacokinetic differences due to race have not been studied.

Adolescents and Pediatric Patients
Pharmacokinetic studies evaluated the systemic exposure of the 4-mg oral granule formulation in pediatric patients 6 to 23 months of age, the 4-mg chewable tablets in pediatric patients 2 to 5 years of age, the 5-mg chewable tablets in pediatric patients 6 to 14 years of age, and the 10-mg film-coated tablets in young adults and adolescents ≥15 years of age.

The plasma concentration profile of montelukast following administration of the 10-mg film-coated tablet is similar in adolescents ≥15 years of age and young adults. The 10-mg film-coated tablet is recommended for use in patients ≥15 years of age.

The mean systemic exposure of the 4-mg chewable tablet in pediatric patients 2 to 5 years of age and the 5-mg chewable tablets in pediatric patients 6 to 14 years of age is similar to the mean systemic exposure of the 10-mg film-coated tablet in adults. The 5-mg chewable tablet should be used in pediatric patients 6 to 14 years of age and the 4-mg chewable tablet should be used in pediatric patients 2 to 5 years of age.

In children 6 to 11 months of age, the systemic exposure to montelukast and the variability of plasma montelukast concentrations were higher than those observed in adults. Based on population analyses, the mean AUC (4296 ng•hr/mL [range 1200 to 7153]) was 60% higher and the mean Cmax (667 ng/mL [range 201 to 1058]) was 89% higher than those observed in adults (mean AUC 2689 ng•hr/mL [range 1521 to 4595]) and mean Cmax (353 ng/mL [range 180 to 548]). The systemic exposure in children 12 to 23 months of age was less variable, but was still higher than that observed in adults. The mean AUC (3574 ng•hr/mL [range 2229 to 5408]) was 33% higher and the mean Cmax (562 ng/mL [range 296 to 814]) was 60% higher than those observed in adults. Safety and tolerability of montelukast in a single-dose pharmacokinetic study in 26 children 6 to 23 months of age were similar to that of patients two years and above [see Adverse Reactions (6.1)]. The 4-mg oral granule formulation should be used for pediatric patients 12 to 23 months of age for the treatment of asthma, or for pediatric patients 6 to 23 months of age for the treatment of perennial allergic rhinitis. Since the 4-mg oral granule formulation is bioequivalent to the 4-mg chewable tablet, it can also be used as an alternative formulation to the 4-mg chewable tablet in pediatric patients 2 to 5 years of age.

Drug Interaction Studies

Theophylline, Prednisone, and Prednisolone
SINGULAIR has been administered with other therapies routinely used in the prophylaxis and chronic treatment of asthma with no apparent increase in adverse reactions. In drug-interaction studies, the recommended clinical dose of montelukast did not have clinically important effects on the pharmacokinetics of the following drugs: theophylline, prednisone, and prednisolone.

Montelukast at a dose of 10 mg once daily dosed to pharmacokinetic steady state, did not cause clinically significant changes in the kinetics of a single intravenous dose of theophylline [predominantly a cytochrome P450 (CYP) 1A2 substrate]. Montelukast at doses of ≥100 mg daily dosed to pharmacokinetic steady state, did not cause any clinically significant change in plasma profiles of prednisone or prednisolone following administration of either oral prednisone or intravenous prednisolone.

Oral Contraceptives, fexofenadine, Digoxin, and Warfarin
In drug interaction studies, the recommended clinical dose of montelukast did not have clinically important effects on the pharmacokinetics of the following drugs: oral contraceptives (norethindrone 1 mg/ethinyl estradiol 35 mcg), digoxin, and warfarin. Montelukast at doses of ≥100 mg daily dosed to pharmacokinetic steady state did not significantly alter the plasma concentrations of either component of an oral contraceptive containing norethindrone 1 mg/ethinyl estradiol 35 mcg. Montelukast at a dose of 10 mg once daily dosed to pharmacokinetic steady state did not change the plasma concentration profile of fexofenadine, did not change the pharmacokinetic profile or urinary excretion of immunoreactive digoxin; did not change the pharmacokinetic profile of warfarin (primarily a substrate of CYP2C9, 3A4 and 1A2) or influence the effect of a single 30-mg oral dose of warfarin on prothrombin time or the International Normalized Ratio (INR).

Thyroid Hormones, Sedative Hypnotics, Non-Steroidal Anti-Inflammatory Agents, Benzodiazepines, and Decongestants
Although additional specific interaction studies were not performed, SINGULAIR was used concomitantly with a wide range of commonly prescribed drugs in clinical studies without evidence of clinical adverse interactions. These medications included thyroid hormones, sedative hypnotics, non-steroidal anti-inflammatory agents, benzodiazepines, and decongestants.

Cytochrome P450 (CYP) Enzyme Inducers
Phenobarbital, which induces hepatic metabolism, decreased the area under the plasma concentration curve (AUC) of montelukast approximately 40% following a single 10-mg dose of montelukast. No dosage adjustment for SINGULAIR is recommended. It is reasonable to employ appropriate clinical monitoring when potent CYP enzyme inducers, such as phenobarbital or rifampin, are co-administered with SINGULAIR.

Effect of Montelukast on Cytochrome P450 (CYP) Enzymes
Montelukast is a potent inhibitor of CYP2C8 in vitro. However, data from a clinical drug-drug interaction study involving montelukast and rosiglitazone (a probe substrate representative of drugs primarily metabolized by CYP2C8) in 12 healthy individuals demonstrated that the pharmacokinetics of rosiglitazone are not altered when the drugs are coadministered, indicating that montelukast does not inhibit CYP2C8 in vivo. Therefore, montelukast is not anticipated to alter the metabolism of drugs metabolized by this enzyme (e.g., paclitaxel, rosiglitazone, and repaglinide). Based on further in vitro results in human liver microsomes, therapeutic plasma concentrations of montelukast do not inhibit CYP 3A4, 2C9, 1A2, 2A6, 2C19, or 2D6.

Cytochrome P450 (CYP) Enzyme Inhibitors
In vitro studies have shown that montelukast is a substrate of CYP 2C8, 2C9, and 3A4. Co-administration of montelukast with itraconazole, a strong CYP 3A4 inhibitor, resulted in no significant increase in the systemic exposure of montelukast. Data from a clinical drug interaction study involving montelukast and gemfibrozil (an inhibitor of both CYP 2C8 and 2C9) demonstrated that gemfibrozil, at a therapeutic dose, increased the systemic exposure of montelukast by 4.4-fold. Co-administration of itraconazole, gemfibrozil, and montelukast did not further increase the systemic exposure of montelukast. Based on available clinical experience, no dosage adjustment of montelukast is required upon co-administration with gemfibrozil [see Overdosage (10)].

13 NONCLINICAL TOXICOLOGY

13.1 Carcinogenesis, Mutagenesis, Impairment of Fertility

No evidence of tumorigenicity was seen in carcinogenicity studies of either 2 years in Sprague-Dawley rats or 92 weeks in mice at oral gavage doses up to 200 mg/kg/day or 100 mg/kg/day, respectively. The estimated exposure in rats was approximately 120 and 75 times the AUC for adults and children, respectively, at the maximum recommended daily oral dose. The estimated exposure in mice was approximately 45 and 25 times the AUC for adults and children, respectively, at the maximum recommended daily oral dose.

Montelukast demonstrated no evidence of mutagenic or clastogenic activity in the following assays: the microbial mutagenesis assay, the V-79 mammalian cell mutagenesis assay, the alkaline elution assay in rat hepatocytes, the chromosomal aberration assay in Chinese hamster ovary cells, and in the in vivo mouse bone marrow chromosomal aberration assay.

In fertility studies in female rats, montelukast produced reductions in fertility and fecundity indices at an oral dose of 200 mg/kg (estimated exposure was approximately 70 times the AUC for adults at the maximum recommended daily oral dose). No effects on female fertility or fecundity were observed at an oral dose of 100 mg/kg (estimated exposure was approximately 20 times the AUC for adults at the maximum recommended daily oral dose). Montelukast had no effects on fertility in male rats at oral doses up to 800 mg/kg (estimated exposure was approximately 160 times the AUC for adults at the maximum recommended daily oral dose).

14 CLINICAL STUDIES

14.1 Asthma

Adults and Adolescents 15 Years of Age and Older with Asthma

Clinical trials in adults and adolescents 15 years of age and older demonstrated there is no additional clinical benefit to montelukast doses above 10 mg once daily.

The efficacy of SINGULAIR for the chronic treatment of asthma in adults and adolescents 15 years of age and older was demonstrated in two (U.S. and Multinational) similarly designed, randomized, 12-week, double-blind, placebo-controlled trials in 1576 patients (795 treated with SINGULAIR, 530 treated with placebo, and 251 treated with active control). The median age was 33 years (range 15 to 85); 56.8% were females and 43.2% were males. The ethnic/racial distribution in these studies was 71.6% Caucasian, 17.7% Hispanic, 7.2% other origins and 3.5% Black. Patients had mild or moderate asthma and were non-smokers who required approximately 5 puffs of inhaled β-agonist per day on an "as-needed" basis. The patients had a mean baseline percent of predicted forced expiratory volume in 1 second (FEV1) of 66% (approximate range, 40 to 90%). The co-primary endpoints in these trials were FEV1 and daytime asthma symptoms. In both studies after 12 weeks, a random subset of patients receiving SINGULAIR was switched to placebo for an additional 3 weeks of double-blind treatment to evaluate for possible rebound effects.

The results of the U.S. trial on the primary endpoint, morning FEV1, expressed as mean percent change from baseline averaged over the 12-week treatment period, are shown in FIGURE 2. Compared with placebo, treatment with one SINGULAIR 10-mg tablet daily in the evening resulted in a statistically significant increase in FEV1 percent change from baseline (13.0%-change in the group treated with SINGULAIR vs. 4.2%-change in the placebo group, p<0.001); the change from baseline in FEV1 for SINGULAIR was 0.32 liters compared with 0.10 liters for placebo, corresponding to a between-group difference of 0.22 liters (p<0.001, 95% CI 0.17 liters, 0.27 liters). The results of the Multinational trial on FEV1 were similar.

Figure 2: FEV1 Mean Percent Change from Baseline (U.S. Trial: SINGULAIR N=406; Placebo N=270) (ANOVA Model)

The effect of SINGULAIR on other primary and secondary endpoints, represented by the Multinational study is shown in TABLE 6. Results on these endpoints were similar in the US study.

Table 6: Effect of SINGULAIR on Primary and Secondary Endpoints in a Multinational Placebo-controlled Trial (ANOVA Model)
 | SINGULAIR |  |  | Placebo
Endpoint | N | Baseline | Mean Change from Baseline | N | Baseline | Mean Change from Baseline
Daytime Asthma Symptoms (0 to 6 scale) | 372 | 2.35 | -0.49 [p<0.001, compared with placebo] | 245 | 2.40 | -0.26
β-agonist (puffs per day) | 371 | 5.35 | -1.65 | 241 | 5.78 | -0.42
AM PEFR (L/min) | 372 | 339.57 | 25.03 | 244 | 335.24 | 1.83
PM PEFR (L/min) | 372 | 355.23 | 20.13 | 244 | 354.02 | -0.49
Nocturnal Awakenings (#/week) | 285 | 5.46 | -2.03 | 195 | 5.57 | -0.78

Both studies evaluated the effect of SINGULAIR on secondary outcomes, including asthma attack (utilization of health-care resources such as an unscheduled visit to a doctor's office, emergency room, or hospital; or treatment with oral, intravenous, or intramuscular corticosteroid), and use of oral corticosteroids for asthma rescue. In the Multinational study, significantly fewer patients (15.6% of patients) on SINGULAIR experienced asthma attacks compared with patients on placebo (27.3%, p<0.001). In the US study, 7.8% of patients on SINGULAIR and 10.3% of patients on placebo experienced asthma attacks, but the difference between the two treatment groups was not significant (p=0.334). In the Multinational study, significantly fewer patients (14.8% of patients) on SINGULAIR were prescribed oral corticosteroids for asthma rescue compared with patients on placebo (25.7%, p<0.001). In the US study, 6.9% of patients on SINGULAIR and 9.9% of patients on placebo were prescribed oral corticosteroids for asthma rescue, but the difference between the two treatment groups was not significant (p=0.196).

Onset of Action and Maintenance of Effects

In each placebo-controlled trial in adults, the treatment effect of SINGULAIR, measured by daily diary card parameters, including symptom scores, "as-needed" β-agonist use, and PEFR measurements, was achieved after the first dose and was maintained throughout the dosing interval (24 hours). No significant change in treatment effect was observed during continuous once-daily evening administration in non-placebo-controlled extension trials for up to one year. Withdrawal of SINGULAIR in asthmatic patients after 12 weeks of continuous use did not cause rebound worsening of asthma.

Pediatric Patients 6 to 14 Years of Age with Asthma

The efficacy of SINGULAIR in pediatric patients 6 to 14 years of age was demonstrated in one 8-week, double-blind, placebo-controlled trial in 336 patients (201 treated with SINGULAIR and 135 treated with placebo) using an inhaled β-agonist on an "as-needed" basis. The patients had a mean baseline percent predicted FEV1 of 72% (approximate range, 45 to 90%) and a mean daily inhaled β-agonist requirement of 3.4 puffs of albuterol. Approximately 36% of the patients were on inhaled corticosteroids. The median age was 11 years (range 6 to 15); 35.4% were females and 64.6% were males. The ethnic/racial distribution in this study was 80.1% Caucasian, 12.8% Black, 4.5% Hispanic, and 2.7% other origins.

Compared with placebo, treatment with one 5-mg SINGULAIR chewable tablet daily resulted in a significant improvement in mean morning FEV1 percent change from baseline (8.7% in the group treated with SINGULAIR vs. 4.2% change from baseline in the placebo group, p<0.001). There was a significant decrease in the mean percentage change in daily "as-needed" inhaled β-agonist use (11.7% decrease from baseline in the group treated with SINGULAIR vs. 8.2% increase from baseline in the placebo group, p<0.05). This effect represents a mean decrease from baseline of 0.56 and 0.23 puffs per day for the montelukast and placebo groups, respectively. Subgroup analyses indicated that younger pediatric patients aged 6 to 11 had efficacy results comparable to those of the older pediatric patients aged 12 to 14.

Similar to the adult studies, no significant change in the treatment effect was observed during continuous once-daily administration in one open-label extension trial without a concurrent placebo group for up to 6 months.

Pediatric Patients 2 to 5 Years of Age with Asthma

The efficacy of SINGULAIR for the chronic treatment of asthma in pediatric patients 2 to 5 years of age was explored in a 12-week, placebo-controlled safety and tolerability study in 689 patients, 461 of whom were treated with SINGULAIR. The median age was 4 years (range 2 to 6); 41.5% were females and 58.5% were males. The ethnic/racial distribution in this study was 56.5% Caucasian, 20.9% Hispanic, 14.4% other origins, and 8.3% Black.

While the primary objective was to determine the safety and tolerability of SINGULAIR in this age group, the study included exploratory efficacy evaluations, including daytime and overnight asthma symptom scores, β-agonist use, oral corticosteroid rescue, and the physician's global evaluation. The findings of these exploratory efficacy evaluations, along with pharmacokinetics and extrapolation of efficacy data from older patients, support the overall conclusion that SINGULAIR is efficacious in the maintenance treatment of asthma in patients 2 to 5 years of age.

Effects in Patients on Concomitant Inhaled Corticosteroids

Separate trials in adults evaluated the ability of SINGULAIR to add to the clinical effect of inhaled corticosteroids and to allow inhaled corticosteroid tapering when used concomitantly.

One randomized, placebo-controlled, parallel-group trial (n=226) enrolled adults with stable asthma with a mean FEV1 of approximately 84% of predicted who were previously maintained on various inhaled corticosteroids (delivered by metered-dose aerosol or dry powder inhalers). The median age was 41.5 years (range 16 to 70); 52.2% were females and 47.8% were males. The ethnic/racial distribution in this study was 92.0% Caucasian, 3.5% Black, 2.2% Hispanic, and 2.2% Asian. The types of inhaled corticosteroids and their mean baseline requirements included beclomethasone dipropionate (mean dose, 1203 mcg/day), triamcinolone acetonide (mean dose, 2004 mcg/day), flunisolide (mean dose, 1971 mcg/day), fluticasone propionate (mean dose, 1083 mcg/day), or budesonide (mean dose, 1192 mcg/day). Some of these inhaled corticosteroids were non-U.S.-approved formulations, and doses expressed may not be ex-actuator. The pre-study inhaled corticosteroid requirements were reduced by approximately 37% during a 5- to 7-week placebo run-in period designed to titrate patients toward their lowest effective inhaled corticosteroid dose. Treatment with SINGULAIR resulted in a further 47% reduction in mean inhaled corticosteroid dose compared with a mean reduction of 30% in the placebo group over the 12-week active treatment period (p≤0.05). It is not known whether the results of this study can be generalized to patients with asthma who require higher doses of inhaled corticosteroids or systemic corticosteroids.

In another randomized, placebo-controlled, parallel-group trial (n=642) in a similar population of adult patients previously maintained, but not adequately controlled, on inhaled corticosteroids (beclomethasone 336 mcg/day), the addition of SINGULAIR to beclomethasone resulted in statistically significant improvements in FEV1 compared with those patients who were continued on beclomethasone alone or those patients who were withdrawn from beclomethasone and treated with montelukast or placebo alone over the last 10 weeks of the 16-week, blinded treatment period. Patients who were randomized to treatment arms containing beclomethasone had statistically significantly better asthma control than those patients randomized to SINGULAIR alone or placebo alone as indicated by FEV1, daytime asthma symptoms, PEFR, nocturnal awakenings due to asthma, and "as-needed" β-agonist requirements.

In adult patients with asthma with documented aspirin sensitivity, nearly all of whom were receiving concomitant inhaled and/or oral corticosteroids, a 4-week, randomized, parallel-group trial (n=80) demonstrated that SINGULAIR, compared with placebo, resulted in significant improvement in parameters of asthma control. The magnitude of effect of SINGULAIR in aspirin-sensitive patients was similar to the effect observed in the general population of asthma patients studied. The effect of SINGULAIR on the bronchoconstrictor response to aspirin or other non-steroidal anti-inflammatory drugs in aspirin-sensitive asthmatic patients has not been evaluated [see Warnings and Precautions (5.4)].

14.2 Exercise-Induced Bronchoconstriction (EIB)

Exercise-Induced Bronchoconstriction (Adults, Adolescents, and Pediatric Patients 6 years of age and older)

The efficacy of SINGULAIR, 10 mg, when given as a single dose 2 hours before exercise for the prevention of EIB was investigated in three (U.S. and Multinational), randomized, double-blind, placebo-controlled crossover studies that included a total of 160 adult and adolescent patients 15 years of age and older with EIB. Exercise challenge testing was conducted at 2 hours, 8.5 or 12 hours, and 24 hours following administration of a single dose of study drug (SINGULAIR 10 mg or placebo). The primary endpoint was the mean maximum percent fall in FEV1 following the 2 hours post-dose exercise challenge in all three studies (Study A, Study B, and Study C). In Study A, a single dose of SINGULAIR 10 mg demonstrated a statistically significant protective benefit against EIB when taken 2 hours prior to exercise. Some patients were protected from EIB at 8.5 and 24 hours after administration; however, some patients were not. The results for the mean maximum percent fall at each timepoint in Study A are shown in TABLE 7 and are representative of the results from the other two studies.

Table 7: Mean Maximum Percent Fall in FEV1 Following Exercise Challenge in Study A (N=47) ANOVA Model
Time of exercise challenge following medication administration | Mean Maximum percent fall in FEV1 [Least squares-mean] |  | Treatment difference % for SINGULAIR versus Placebo (95% CI)
 | SINGULAIR | Placebo
2 hours | 13 | 22 | -9 (-12, -5)
8.5 hours | 12 | 17 | -5 (-9, -2)
24 hours | 10 | 14 | -4 (-7, -1)

The efficacy of SINGULAIR 5-mg chewable tablets, when given as a single dose 2 hours before exercise for the prevention of EIB, was investigated in one multinational, randomized, double-blind, placebo-controlled crossover study that included a total of 64 pediatric patients 6 to 14 years of age with EIB. Exercise challenge testing was conducted at 2 hours and 24 hours following administration of a single dose of study drug (SINGULAIR 5 mg or placebo). The primary endpoint was the mean maximum percent fall in FEV1 following the 2 hours post-dose exercise challenge. A single dose of SINGULAIR 5 mg demonstrated a statistically significant protective benefit against EIB when taken 2 hours prior to exercise (TABLE 8). Similar results were shown at 24 hours post-dose (a secondary endpoint). Some patients were protected from EIB at 24 hours after administration; however, some patients were not. No timepoints were assessed between 2 and 24 hours post-dose.

Table 8: Mean Maximum Percent Fall in FEV1 Following Exercise Challenge in Pediatric Patients (N=64) ANOVA Model
Time of exercise challenge following medication administration | Mean Maximum percent fall in FEV1 [Least squares-mean] |  | Treatment difference % for SINGULAIR versus Placebo (95% CI)
 | SINGULAIR | Placebo
2 hours | 15 | 20 | -5 (-9, -1)
24 hours | 13 | 17 | -4 (-7, -1)

The efficacy of SINGULAIR for prevention of EIB in patients below 6 years of age has not been established.

Daily administration of SINGULAIR for the chronic treatment of asthma has not been established to prevent acute episodes of EIB.

In a 12-week, randomized, double-blind, parallel group study of 110 adult and adolescent asthmatics 15 years of age and older, with a mean baseline FEV1 percent of predicted of 83% and with documented exercise-induced exacerbation of asthma, treatment with SINGULAIR, 10 mg, once daily in the evening, resulted in a statistically significant reduction in mean maximal percent fall in FEV1 and mean time to recovery to within 5% of the pre-exercise FEV1. Exercise challenge was conducted at the end of the dosing interval (i.e., 20 to 24 hours after the preceding dose). This effect was maintained throughout the 12-week treatment period indicating that tolerance did not occur. SINGULAIR did not, however, prevent clinically significant deterioration in maximal percent fall in FEV1 after exercise (i.e., ≥20% decrease from pre-exercise baseline) in 52% of patients studied. In a separate crossover study in adults, a similar effect was observed after two once-daily 10-mg doses of SINGULAIR.

In pediatric patients 6 to 14 years of age, using the 5-mg chewable tablet, a 2-day crossover study demonstrated effects similar to those observed in adults when exercise challenge was conducted at the end of the dosing interval (i.e., 20 to 24 hours after the preceding dose).

14.3 Allergic Rhinitis (Seasonal and Perennial)

Seasonal Allergic Rhinitis

The efficacy of SINGULAIR tablets for the treatment of seasonal allergic rhinitis was investigated in 5 similarly designed, randomized, double-blind, parallel-group, placebo- and active-controlled (loratadine) trials conducted in North America. The 5 trials enrolled a total of 5029 patients, of whom 1799 were treated with SINGULAIR tablets. Patients were 15 to 82 years of age with a history of seasonal allergic rhinitis, a positive skin test to at least one relevant seasonal allergen, and active symptoms of seasonal allergic rhinitis at study entry.

The period of randomized treatment was 2 weeks in 4 trials and 4 weeks in one trial. The primary outcome variable was mean change from baseline in daytime nasal symptoms score (the average of individual scores of nasal congestion, rhinorrhea, nasal itching, sneezing) as assessed by patients on a 0-3 categorical scale.

Four of the five trials showed a significant reduction in daytime nasal symptoms scores with SINGULAIR 10-mg tablets compared with placebo. The results of one trial are shown below. The median age in this trial was 35.0 years (range 15 to 81); 65.4% were females and 34.6% were males. The ethnic/racial distribution in this study was 83.1% Caucasian, 6.4% other origins, 5.8% Black, and 4.8% Hispanic. The mean changes from baseline in daytime nasal symptoms score in the treatment groups that received SINGULAIR tablets, loratadine, and placebo are shown in TABLE 9. The remaining three trials that demonstrated efficacy showed similar results. Efficacy was demonstrated for seasonal allergic rhinitis when montelukast was administered in the morning or the evening.

Table 9: Effects of SINGULAIR on Daytime Nasal Symptoms Score [Average of individual scores of nasal congestion, rhinorrhea, nasal itching, sneezing as assessed by patients on a 0-3 categorical scale.] in a Placebo- and Active-controlled Trial in Patients with Seasonal Allergic Rhinitis (ANCOVA Model)
Treatment Group (N) | Baseline Mean Score | Mean Change from Baseline | Difference Between Treatment and Placebo (95% CI) Least-Squares Mean
SINGULAIR 10 mg (344) | 2.09 | -0.39 | -0.13 [Statistically different from placebo (p≤0.001).] (-0.21, -0.06)
Placebo (351) | 2.10 | -0.26 | N.A.
Active Control [The study was not designed for statistical comparison between SINGULAIR and the active control (loratadine).] (Loratadine 10 mg) (599) | 2.06 | -0.46 | -0.24 (-0.31, -0.17)

Perennial Allergic Rhinitis

The efficacy of SINGULAIR tablets for the treatment of perennial allergic rhinitis was investigated in 2 randomized, double-blind, placebo-controlled studies conducted in North America and Europe. The two studies enrolled a total of 3357 patients, of whom 1632 received SINGULAIR 10-mg tablets. Patients 15 to 82 years of age with perennial allergic rhinitis as confirmed by history and a positive skin test to at least one relevant perennial allergen (dust mites, animal dander, and/or mold spores), who had active symptoms at the time of study entry, were enrolled.

In the study in which efficacy was demonstrated, the median age was 35 years (range 15 to 81); 64.1% were females and 35.9% were males. The ethnic/racial distribution in this study was 83.2% Caucasian, 8.1% Black, 5.4% Hispanic, 2.3% Asian, and 1.0% other origins. SINGULAIR 10-mg tablets once daily was shown to significantly reduce symptoms of perennial allergic rhinitis over a 6-week treatment period (TABLE 10); in this study the primary outcome variable was mean change from baseline in daytime nasal symptoms score (the average of individual scores of nasal congestion, rhinorrhea, and sneezing).

Table 10: Effects of SINGULAIR on Daytime Nasal Symptoms Score [Average of individual scores of nasal congestion, rhinorrhea, sneezing as assessed by patients on a 0-3 categorical scale.] in a Placebo-controlled Trial in Patients with Perennial Allergic Rhinitis (ANCOVA Model)
Treatment Group (N) | Baseline Mean Score | Mean Change from Baseline | Difference Between Treatment and Placebo (95% CI) Least-Squares Mean
SINGULAIR 10 mg (1000) | 2.09 | -0.42 | -0.08 [Statistically different from placebo (p≤0.001).] (-0.12, -0.04)
Placebo (980) | 2.10 | -0.35 | N.A.

The other 6-week study evaluated SINGULAIR 10 mg (n=626), placebo (n=609), and an active-control (cetirizine 10 mg; n=120). The primary analysis compared the mean change from baseline in daytime nasal symptoms score for SINGULAIR vs. placebo over the first 4 weeks of treatment; the study was not designed for statistical comparison between SINGULAIR and the active-control. The primary outcome variable included nasal itching in addition to nasal congestion, rhinorrhea, and sneezing. The estimated difference between SINGULAIR and placebo was -0.04 with a 95% CI of (-0.09, 0.01). The estimated difference between the active-control and placebo was -0.10 with a 95% CI of (-0.19, -0.01).

16 HOW SUPPLIED/STORAGE AND HANDLING

SINGULAIR 4 mg Oral Granules: white granules with 500 mg net weight, packed in a child-resistant foil packet.

NDC 78206-171-01 unit of use carton with 30 packets.

SINGULAIR 4 mg Tablets: pink, oval, bi-convex-shaped chewable tablets, with code MSD 711 on one side and SINGULAIR on the other.

NDC 78206-170-01 unit of use high-density polyethylene (HDPE) bottles of 30 with a polypropylene child-resistant cap, an aluminum foil induction seal, and silica gel desiccant.

SINGULAIR 5 mg Tablets: pink, round, bi-convex-shaped chewable tablets, with code MSD 275 on one side and SINGULAIR on the other.

NDC 78206-173-01 unit of use high-density polyethylene (HDPE) bottles of 30 with a polypropylene child-resistant cap, an aluminum foil induction seal, and silica gel desiccant.

SINGULAIR 10 mg Tablets: beige, rounded square-shaped, film-coated tablets, with code MSD 117 on one side and SINGULAIR on the other.

NDC 78206-172-01 unit of use high-density polyethylene (HDPE) bottles of 30 with a polypropylene child-resistant cap, an aluminum foil induction seal, and silica gel desiccant

NDC 78206-172-02 unit of use high-density polyethylene (HDPE) bottles of 90 with a polypropylene child-resistant cap, an aluminum foil induction seal, and silica gel desiccant.

Storage

Store SINGULAIR 4-mg oral granules, 4-mg chewable tablets, 5-mg chewable tablets and 10-mg film-coated tablets at 20°C to 25°C (68°F to 77°F), excursions permitted to 15°C to 30°C (59°F to 86°F) [see USP Controlled Room Temperature]. Protect from moisture and light. Store in original package.

17 PATIENT COUNSELING INFORMATION

For the tablets and chewable tablets, advise the patient and/or caregiver to read the FDA-approved patient labeling (Medication Guide).

For the oral granules, advise the patient and/or caregiver to read the FDA-approved patient labeling (Medication Guide and Instructions for Use).

- Advise patients about the potential risk for serious neuropsychiatric symptoms and behavioral changes with SINGULAIR use [see Warnings and Precautions (5.1)].
- Discuss the benefits and risks of SINGULAIR with patients when prescribing or continuing treatment with SINGULAIR [see Warnings and Precautions (5.1)].
- Advise patients to monitor for changes in behavior or neuropsychiatric symptoms in patients taking SINGULAIR [see Warnings and Precautions (5.1)].
- Instruct patients to discontinue SINGULAIR and contact a healthcare provider immediately if changes in behavior or thinking that are not typical for the patient occur, or if the patient develops suicidal ideation or suicidal behavior [see Warnings and Precautions (5.1)].
- Advise patients to take SINGULAIR daily as prescribed, even when they are asymptomatic, as well as during periods of worsening asthma, and to contact their physicians if their asthma is not well controlled.
- Advise patients that oral SINGULAIR is not for the treatment of acute asthma attacks. They should have appropriate short-acting inhaled β-agonist medication available to treat asthma exacerbations. Patients who have exacerbations of asthma after exercise should be instructed to have available for rescue a short-acting inhaled β-agonist. Daily administration of SINGULAIR for the chronic treatment of asthma has not been established to prevent acute episodes of EIB [see Warnings and Precautions (5.2)].
- Advise patients to seek medical attention if short-acting inhaled bronchodilators are needed more often than usual, or if more than the maximum number of inhalations of short-acting bronchodilator treatment prescribed for a 24-hour period are needed.
- Instruct patients to continue other anti-asthma medications as prescribed unless instructed by a physician.
- Instruct patients with known aspirin sensitivity to continue avoidance of aspirin or non-steroidal anti-inflammatory agents while taking SINGULAIR [see Warnings and Precautions (5.4)].
- Inform phenylketonuric patients that the 4-mg and 5-mg chewable tablets contain phenylalanine (a source of aspartame) [see Warnings and Precautions (5.6)].

Dist. by: Organon LLC, a subsidiary of
ORGANON & Co.,
Jersey City, NJ 07302, USA

For patent information: www.organon.com/our-solutions/patent/

Copyright © 2021 Organon Global Inc.
All rights reserved.

uspi-og0476-mf-2106r001

MEDICATION GUIDE
SINGULAIR® (SING-u-lair)
(montelukast sodium)

tablets

chewable tablets

oral granules

What is the most important information I should know about SINGULAIR?

Serious mental health problems have happened in people taking SINGULAIR or even after treatment has stopped. This can happen in people with or without a history of mental health problems. Stop taking SINGULAIR and tell your healthcare provider right away if you or your child have any unusual changes in behavior or thinking, including any of these symptoms:

- agitation, including aggressive
  behavior or hostility
- attention problems
- bad or vivid dreams
- depression
- disorientation (confusion)
- feeling anxious
- irritability

- hallucinations (seeing or hearing
  things that are not really there)
- memory problems
- obsessive-compulsive symptoms
- restlessness
- sleep walking
- stuttering

- suicidal thoughts and actions
  (including suicide)
- tremor
- trouble sleeping
- uncontrolled muscle movements

What is SINGULAIR?

SINGULAIR is a prescription medicine that blocks substances in the body called leukotrienes. This may help to improve symptoms of asthma and inflammation of the lining of the nose (allergic rhinitis). SINGULAIR does not contain a steroid. SINGULAIR is used to:

1. Prevent asthma attacks and for the long-term treatment of asthma in adults and children ages 12 months and older. Do not take SINGULAIR if you need relief right away for a sudden asthma attack. If you have an asthma attack, you should follow the instructions your healthcare provider gave you for treating asthma attacks.
2. Prevent exercise-induced asthma in people 6 years of age and older.
3. Help control the symptoms of allergic rhinitis such as sneezing, stuffy nose, runny nose, and itching of the nose. SINGULAIR is used to treat the following in people who have already taken other medicines that did not work well enough or in people who could not tolerate other medicines:
  - outdoor allergies that happen part of the year (seasonal allergic rhinitis) in adults and children ages 2 years and older, and
  - indoor allergies that happen all year (perennial allergic rhinitis) in adults and children ages 6 months and older.

Do not take SINGULAIR if you are allergic to any of its ingredients. See the end of this Medication Guide for a complete list of the ingredients in SINGULAIR.

Before taking SINGULAIR, tell your healthcare provider about all your medical conditions, including if you:

- are allergic to aspirin.
- have phenylketonuria. SINGULAIR chewable tablets contain aspartame, a source of phenylalanine.
- have or have had mental health problems.
- are pregnant or plan to become pregnant. Talk to your healthcare provider if you are pregnant or plan to become pregnant, SINGULAIR may not be right for you.
- are breastfeeding or plan to breastfeed. It is not known if SINGULAIR passes into your breast milk. Talk to your healthcare provider about the best way to feed your baby while taking SINGULAIR.

Tell your healthcare provider about all the medicines you take, including prescription and over the counter medicines, vitamins, and herbal supplements. Some medicines may affect how SINGULAIR works, or SINGULAIR may affect how your other medicines work.

How should I take SINGULAIR?

For anyone who takes SINGULAIR:

- Read the detailed Instructions for Use that comes with SINGULAIR oral granules.
- Take SINGULAIR exactly as prescribed by your healthcare provider. Your healthcare provider will tell you how much SINGULAIR to take, and when to take it.
- Stop taking SINGULAIR and tell your healthcare provider right away if you or your child have any unusual changes in behavior or thinking.
- You can take SINGULAIR with food or without food. See the section "How can I give SINGULAIR oral granules to my child?" in the Instructions for Use for information about what foods and liquids can be taken with SINGULAIR oral granules.
- If you or your child misses a dose of SINGULAIR, just take the next dose at your regular time. Do not take 2 doses at the same time.
- If you take too much SINGULAIR, call your healthcare provider right away.

For adults and children 12 months of age and older with asthma:

- Take SINGULAIR 1 time each day, in the evening. Continue to take SINGULAIR every day for as long as your healthcare provider prescribes it, even if you have no asthma symptoms.
- Tell your healthcare provider right away if your asthma symptoms get worse, or if you need to use your rescue inhaler medicine more often for asthma attacks.
- Always have your rescue inhaler medicine with you for asthma attacks.
- Continue to take your other asthma medicines as prescribed unless your healthcare provider tells you to change how you take these medicines.

For people 6 years of age and older for the prevention of exercise-induced asthma:

- Take SINGULAIR at least 2 hours before exercise.
- Always have your rescue inhaler medicine with you for asthma attacks.
- If you take SINGULAIR every day for chronic asthma or allergic rhinitis, do not take another dose to prevent exercise-induced asthma. Talk to your healthcare provider about your treatment for exercise-induced asthma.
- Do not take 2 doses of SINGULAIR within 24 hours (1 day).

For anyone 2 years of age and older with seasonal allergic rhinitis, or for anyone 6 months of age and older with perennial allergic rhinitis:

- Take SINGULAIR 1 time each day, at about the same time each day.

What should I avoid while taking SINGULAIR?

If you have asthma and aspirin makes your asthma symptoms worse, continue to avoid taking aspirin or other medicines called non-steroidal anti-inflammatory drugs (NSAIDs) while taking SINGULAIR.

What are the possible side effects of SINGULAIR?

SINGULAIR may cause serious side effects, including:

- See “What is the most important information I should know about SINGULAIR?”
- Increase in certain white blood cells (eosinophils) and possible inflamed blood vessels throughout the body (systemic vasculitis). Rarely, this can happen in people with asthma who take SINGULAIR. This sometimes happens in people who also take a steroid medicine by mouth that is being stopped or the dose is being lowered.

Tell your healthcare provider right away if you get one or more of these symptoms:

- a feeling of pins and needles or numbness of arms or legs
- a flu-like illness

- rash
- severe inflammation (pain and swelling) of the sinuses (sinusitis)

The most common side effects of SINGULAIR include:

- upper respiratory infection
- fever
- headache
- sore throat

- cough
- stomach pain
- diarrhea
- earache or ear infection

- flu
- runny nose
- sinus infection

These are not all the possible side effects of SINGULAIR. Call your doctor for medical advice about side effects. You may report side effects to FDA at 1-800-FDA-1088.

How should I store SINGULAIR?

- Store SINGULAIR at room temperature between 68°F to 77°F (20°C to 25°C).
- Keep SINGULAIR in the package it comes in.
- Keep SINGULAIR in a dry place and keep it away from light.
- Keep SINGULAIR and all medicines out of reach of children.

General information about the safe and effective use of SINGULAIR.

Medicines are sometimes prescribed for purposes other than those listed in a Medication Guide. Do not use SINGULAIR for a condition for which it was not prescribed. Do not give SINGULAIR to other people even if they have the same symptoms you have. It may harm them.

You can ask your pharmacist or healthcare provider for information about SINGULAIR that is written for health professionals.

What are the ingredients in SINGULAIR?

Active ingredient: montelukast sodium

Inactive ingredients:

- 4-mg oral granules: mannitol, hydroxypropyl cellulose, and magnesium stearate.
- 4-mg and 5-mg chewable tablets: mannitol, microcrystalline cellulose, hydroxypropyl cellulose, red ferric oxide, croscarmellose sodium, cherry flavor, aspartame, and magnesium stearate.
- People with Phenylketonuria: SINGULAIR 4-mg chewable tablets contain 0.674 mg of phenylalanine and SINGULAIR 5-mg chewable tablets contain 0.842 mg of phenylalanine.
- 10-mg tablet: microcrystalline cellulose, lactose monohydrate, croscarmellose sodium, hydroxypropyl cellulose, and magnesium stearate. The film coating contains: hydroxypropyl methylcellulose, hydroxypropyl cellulose, titanium dioxide, red ferric oxide, yellow ferric oxide, and carnauba wax.

Dist. by: Organon LLC, a subsidiary of
ORGANON & Co.,
Jersey City, NJ 07302, USA

For patent information: www.organon.com/our-solutions/patent/

Copyright © 2021 Organon Global Inc.
All rights reserved.

usmg-og0476-mf-2106r000

This Medication Guide has been approved by the U.S. Food and Drug Administration

Revised: 6/2021

INSTRUCTIONS FOR USE

SINGULAIR® (SING-u-lair)
(montelukast sodium)
oral granules

This Instructions for Use contains information on how to use SINGULAIR oral granules.

Important Information:

- Before giving a dose of SINGULAIR oral granules, read this Instructions for Use to be sure you prepare and give the oral granules correctly.
- Give SINGULAIR oral granules to your child exactly as instructed by your healthcare provider.
- Stop giving SINGULAIR and tell your healthcare provider right away if your child has any unusual changes in behavior or thinking.
- Continue to give your child their asthma medicines as prescribed, unless your healthcare provider tells you to change how you give these medicines.
- You can give SINGULAIR oral granules with food or without food.

How can I give SINGULAIR oral granules to my child?

- Do not open the packet until ready to use.
- There are different ways you can give SINGULAIR 4-mg oral granules. You should choose the best method for your child:
  - right into the mouth
  - dissolved in 1 teaspoonful (5 mL) of cold or room temperature baby formula or breast milk
  - mixed with 1 spoonful of one of the following soft foods at cold or room temperature: applesauce, mashed carrots, rice, or ice cream.
- Give the child all of the mixture within 15 minutes.
- Do not store any leftover SINGULAIR mixture (oral granules mixed with food, baby formula, or breast milk) for use at a later time. Throw away any unused portion.
- Do not mix SINGULAIR oral granules with any liquid drink other than baby formula or breast milk. Your child may drink other liquids after swallowing the mixture.

How should I store SINGULAIR?

- Store SINGULAIR at room temperature between 68°F to 77°F (20°C to 25°C).
- Keep SINGULAIR in the package it comes in.
- Keep SINGULAIR in a dry place and keep it away from light.
- Keep SINGULAIR and all medicines out of the reach of children.

Dist. by: Organon LLC, a subsidiary of
ORGANON & Co.,
Jersey City, NJ 07302, USA

For patent information: www.organon.com/our-solutions/patent/
Copyright © 2021 Organon Global Inc.
All rights reserved.
usifu-og0476-og-2106r000
For more information, call 1-844-674-3200

This Instructions for Use has been approved by the U.S. Food and Drug Administration Revised: June 2021

PRINCIPAL DISPLAY PANEL - 4 mg Packet Carton

Singulair® 4 mg
(Montelukast Sodium)
ORAL GRANULES

NDC 78206-171-01

For Pediatric Patients 6 months to 5 years of age.

Dist. by: Organon LLC, a subsidiary of
ORGANON & Co.,
Jersey City, NJ 07302, USA

Manuf. by: Patheon Manufacturing Services LLC
Greenville, NC 27834, USA

Montelukast Sodium (active ingred.) Made in Ireland
Formulated in USA

Attention Health Care Professional: Dispense the enclosed Medication Guide to each patient.

DIRECTIONS FOR USE: See accompanying Prescribing Information. Once opened, use the
contents of this packet within 15 minutes (with or without mixing with food).
Discard any unused portion.

Rx only

PRINCIPAL DISPLAY PANEL - 4 mg Tablet Bottle Label

NDC 78206-170-01

Singulair®
(Montelukast Sodium)
CHEWABLE Tablets

4 mg

Dispense the accompanying Medication Guide
to each patient.

For Pediatric Patients 2-5 Years of Age

Phenylketonurics: contains phenylalanine
(a component of aspartame) 0.674 mg per
4-mg chewable tablet. Each tablet
contains 4.2 mg Montelukast
Sodium equivalent to
4 mg Montelukast.

Rx only 30 Tablets

PRINCIPAL DISPLAY PANEL - 5 mg Tablet Bottle Label

NDC 78206-173-01

Singulair®
(Montelukast Sodium)
CHEWABLE Tablets

5 mg

Dispense the accompanying Medication Guide
to each patient.

For Pediatric Patients 6-14 Years of Age

Phenylketonurics: contains phenylalanine
(a component of aspartame) 0.842 mg per
5-mg chewable tablet. Each tablet
contains 5.2 mg Montelukast
Sodium equivalent to
5 mg Montelukast.

Rx only 30 Tablets

PRINCIPAL DISPLAY PANEL - 10 mg Tablet Bottle Label

NDC 78206-172-01

Singulair®
(Montelukast Sodium)
Tablets

10 mg

Dispense the accompanying Medication Guide
to each patient.

For Adults 15 Years of Age and Older

Each tablet contains 10.4 mg Montelukast Sodium
equivalent to 10 mg Montelukast.

Rx only

30 Tablets